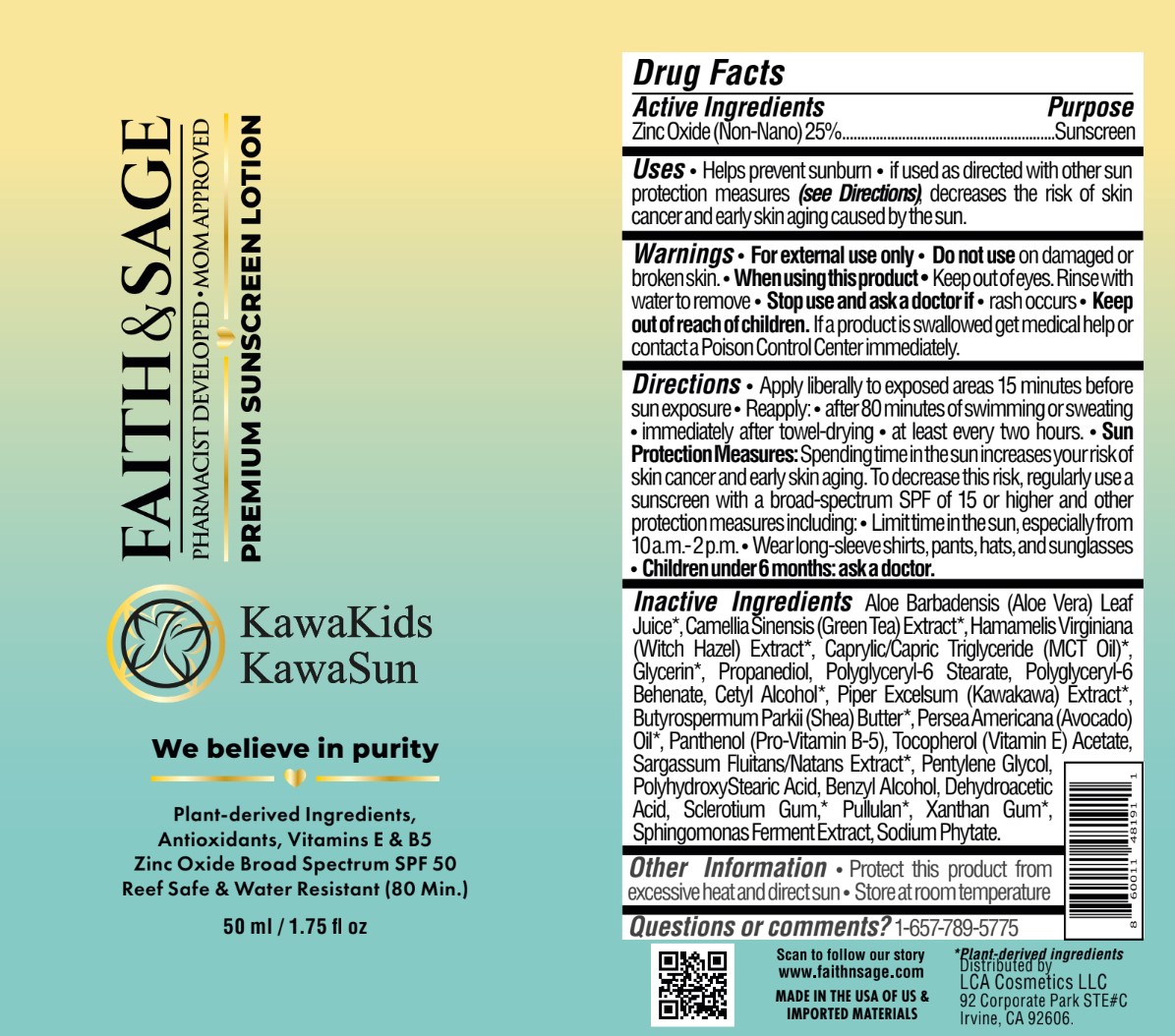 DRUG LABEL: KawaKids KawaSun - Premium Mineral Sunscreen SPF 50
NDC: 84569-123 | Form: LOTION
Manufacturer: LCA COSMETICS LLC
Category: otc | Type: HUMAN OTC DRUG LABEL
Date: 20251212

ACTIVE INGREDIENTS: ZINC OXIDE 250 mg/1 mL
INACTIVE INGREDIENTS: GLYCERIN; POLYGLYCERYL-6 STEARATE; MEDIUM-CHAIN TRIGLYCERIDES; BUTYROSPERMUM PARKII (SHEA) BUTTER UNSAPONIFIABLES; AVOCADO OIL; .ALPHA.-TOCOPHEROL ACETATE; XANTHAN GUM; ALOE VERA LEAF; PANTHENOL; DEHYDROACETIC ACID; GREEN TEA LEAF; HAMAMELIS VIRGINIANA LEAF; PROPANEDIOL; POLYGLYCERYL-6 BEHENATE; CETYL ALCOHOL; PIPER EXCELSUM LEAF; PENTYLENE GLYCOL; POLYHYDROXYSTEARIC ACID (2300 MW); BENZYL ALCOHOL; BETASIZOFIRAN; PULLULAN; PHYTATE SODIUM

KawaKids KawaSun - Premium Mineral Sunscreen SPF 50

Active ingredients

Zinc Oxide 25%

Purpose

Zinc Oxide 25%.............Sunscreen

Uses

- Helps prevent sunburn
- if used as directed with other sun protection measures (see Directions), decreases the risk of skin cancer and early skin aging caused by the sun

Warnings

For external use only

Do not useon damaged or broken skin

When using this product, keep out of eyes. RInse with water to remove.

Stop use and ask a doctor ifrash occurs

Keep out of reach of children.If a product is swallowed get medical help or contact a Poison Control Center immediately.

Directions

- Apply liberally to exposed areas 15 minutes before sun exposure
- Reapply:
- after 80 minutes of swimming or sweating
  - immediately after towel-drying
  - at least every two hours
  - Sun Protection Measures:Spending time in the sun increases your risk of skin cancer and early skin aging. To decrease this risk, regularly use a sunscreen with a broad spectrum SPF of 15 or higher and other protection measures including:
  - Limit time in the sun, especially from 10a.m.-2p.m.
  - Wear long-sleeve shirts, pants, hats, and sunglasses
  - Children under 6 months: ask a doctor.

Inactive Ingredients

Aloe Barbadensis (Aloe Vera) Leaf Juice, Camellia Sinensis (Green Tea) Extract, Hamamelis Virginiana (Witch Hazel) Extract, Caprylic/Capric Trigylceride (MCT Oil), Glycerin, Propanediol, Polyglyceryl-6 Stearate, Polyglyceryl-6 Behenate, Cetyl Alcohol, Piper Excelsum (Kawakawa) Extract, Butyrospermum Parkii (Shea) Butter, Persea Americana (Avocado) Oil, Panthenol (Pro-Vitamin B-5), Tocopherol (Vitamin E) Acetate, Sargassum Fluitans/Natans Extract, Pentylene Glycol, PolyhydroxyStearic Acid, Benzyl Alcohol, Dehydroacetic Acid, Sclerotium Gum, Pullulan, Xanthan Gum, Sphingomonas Ferment Extract, Sodium Phytate.

Other Information

- Protect this product from excessive heat and direct sun
- Store at room temperature

Questions or comments?

1-657-789-5775

PACKAGE LABEL

Faith & Sage

Pharmacist Developed

Mom Approved

Premium Sunscreen Lotion

KawaKids

KawaSun

We believe in purity

Plant-derived Ingredients, Antioxidants, Vitamins E & B5, Zinc Oxide

Broad Spectrum SPF 50

Reef Safe & Water Resistant (80 Min.)

50 mL/1.75 fl oz